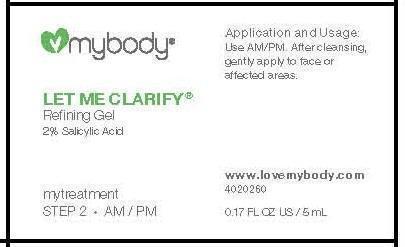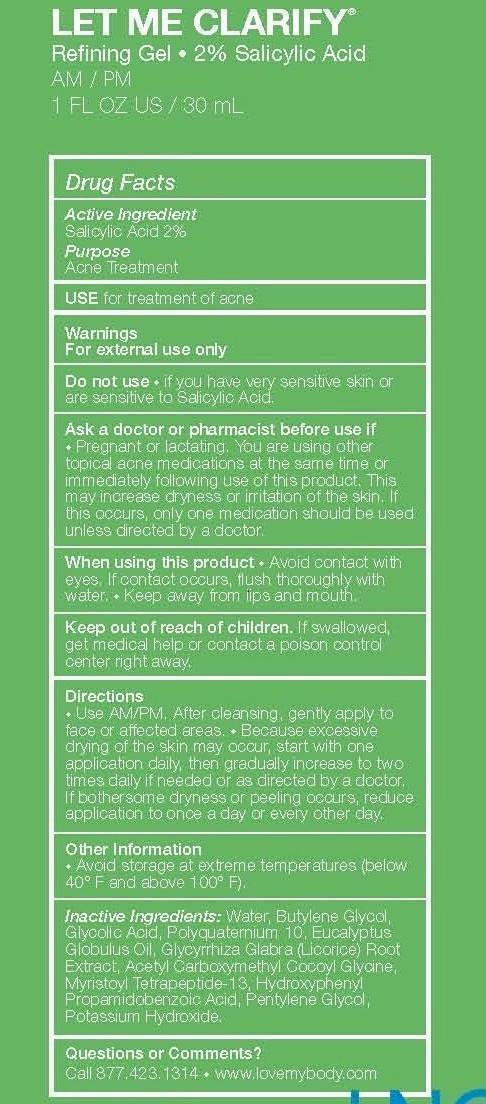 DRUG LABEL: LET ME CLARIFY
NDC: 49520-103 | Form: GEL
Manufacturer: mybody
Category: otc | Type: HUMAN OTC DRUG LABEL
Date: 20131230

ACTIVE INGREDIENTS: SALICYLIC ACID 2 g/100 mL
INACTIVE INGREDIENTS: WATER; 1,3-BUTYLENE GLYCOL; GLYCOLIC ACID; POLYQUATERNIUM-10 (400 CPS AT 2%); EUCALYPTUS GLOBULUS LEAF; GLYCYRRHIZA GLABRA; ACETYL CARBOXYMETHYL COCOYL GLYCINE; MYRISTOYL TETRAPEPTIDE-4; HYDROXYPHENYL PROPAMIDOBENZOIC ACID; PENTYLENE GLYCOL; POTASSIUM HYDROXIDE

ACTIVE INGREDIENTS

SALICYLIC ACID 2%

PURPOSE

ACNE TREATMENT

INDICATIONS AND USAGE

USE FOR THE TREATMENT OF ACNE

WARNINGS

FOR EXTERNAL USE ONLY

DO NOT USE * IF YOU HAVE VERY SENSITIVE SKIN OR ARE SENSITIVE TO SALICYLIC ACID.

ASK A DOCTOR OR PHARMACIST BEFORE USE IF

- PREGNANT OR LACTATING.
- YOU ARE USING OTHER TOPICAL ACNE MEDICATIONS AT THE SAME TIME OR IMMEDIATELY FOLLOWING THE USE OF THIS PRODUCT. THIS MAY INCREASE DRYNESS OR IRRITATION OF THE SKIN. IF THIS OCCURS, ONLY ONE MEDICATION SHOULD BE USED UNLESS DIRECTED BY A DOCTOR.

WHEN USING THIS PRODUCT

- AVOID CONTACT WITH EYES. IF CONTACT OCCURS, FLUSH THOROUGHLY WITH WATER.
- KEEP AWAY FROM LIPS AND MOUTH.

KEEP OUT OF REACH OF CHILDREN. IF SWALLOWED, GET MEDICAL HELP OR CONTACT A POISON CONTROL CENTER RIGHT AWAY.

DIRECTIONS

- USE AM/PM. AFTER CLEANSING, GENTLY APPLY TO FACE OR AFFECTED AREAS.
- BECAUSE EXCESSIVE DRYING OF THE FACE MAY OCCUR, START WITH ONE APPLICATION DAILY IF NEEDED OR AS DIRECTED BY A DOCTOR. IF BOTHERSOME DRYNESS OR PEELING OCCURS, REDUCE APPLICATION TO ONCE A DAY OR EVERY OTHER DAY.

OTHER INFORMATION

* AVOID STORAGE AT EXTREME TEMPERATURES (BELOW 40°F AND ABOVE 100°F).

INACTIVE INGREDIENT

INACTIVE INGREDIENTS: WATER, BUTYLENE GLYCOL, GLYCOLIC ACID, POLYQUATERNIUM 10, EUCALYPTUS GLOBULUS OIL, GLYCYRRHIZA GLABRA (LICORICE) ROOT EXTRACT, ACETYL CARBOXYMETHYL COCOYL GLYCINE, MYRISTOYL TETRAPEPTIDE-13, HYDROXYPHENYL PROPAMIDOBENZOIC ACID, PENTYLENE GLYCOL, POTASSIUM HYDROXIDE.

QUESTIONS OR COMMENTS?

CALL 877.423.1314 * WWW.LOVEMYBODY.COM